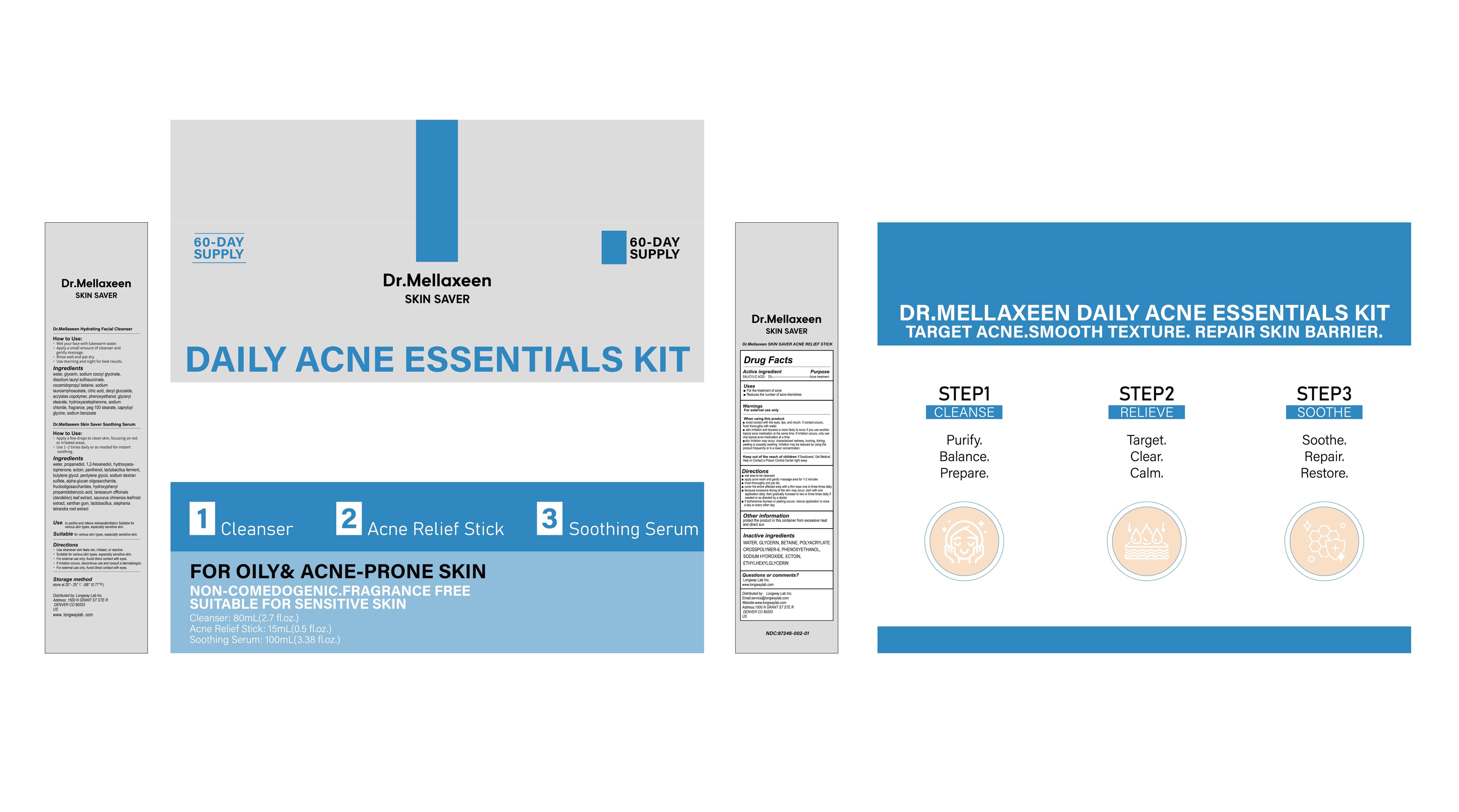 DRUG LABEL: Dr.Mellaxeen SKIN SAVER DAILY ACNE ESSENTIALS Kit
NDC: 85161-134 | Form: STICK
Manufacturer: Longway Technology(Guangzhou)Co.,Ltd.
Category: otc | Type: HUMAN OTC DRUG LABEL
Date: 20251211

ACTIVE INGREDIENTS: SALICYLIC ACID 0.02 g/1 mL
INACTIVE INGREDIENTS: POLYACRYLATE CROSSPOLYMER-6; SODIUM HYDROXIDE; ETHYLHEXYLGLYCERIN; GLYCERIN; BETAINE; ECTOINE; PHENOXYETHANOL; WATER

ACTIVE INGREDIENT

SALICYLIC ACID:2%

PURPOSE

Acne treatment

KEEP OUT OF REACH OF CHILDREN

Keep out of the reach of children lf Swallowed, Get Medical Help or Contact a Poison Control Center right away

QUESTIONS

Longway Lab Inc.
www.longwaylab.com

OTHER SAFETY INFORMATION

protect the product in this container from excessive heat and direct sun

INACTIVE INGREDIENT

WATER,GLYCERIN,BETAINE,POLYACRYLATE CROSSPOLYMER-6,PHENOXYETHANOL,SODIUM HYDROXIDE,ECTOIN,ETHYLHEXYLGLYCERIN

Directions
wet area to be deansed.
apply acne wash and gently massage area for 1-2 minutes.
rinse thoroughly and pat dry.
cover the entire affected area with a thin layer one to three times daily.
because excessive drying of the skin may occur, start with one application daily, then gradually increase to two or three times daily if needed or as directed by a doctor.
if bothersome dryness or peeling occurs, reduce application to once a day or every other day.

Uses
For the treatment of acne
Reduces the number of acne blemishes

WARNINGS

For external use only
When using this product
avoid contact with the eyes, lips, and mouth. lf contact occurs, flush thoroughly with water.
skin irritation and dryness is more likely to occur if you use another topical acne medication at the same time. lf irritation occurs, only use one topical acne medication at a time.
skin irritation may occur, characterized redness, buring, itching,peeling or possibly swelling. lrritation may be reduced by using the product frequently or in a lower concentration.